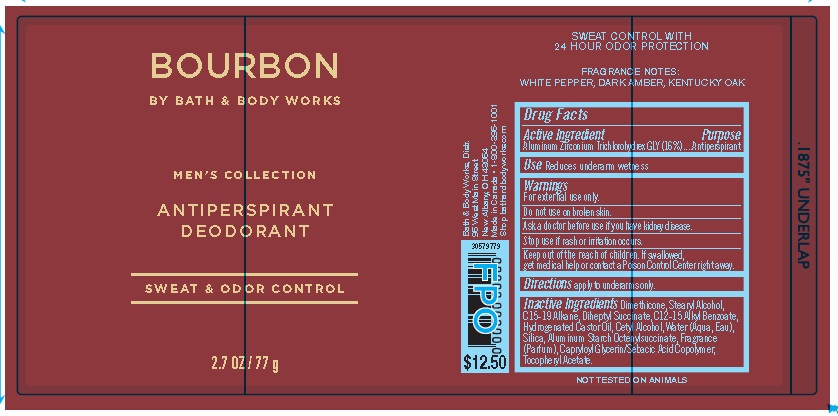 DRUG LABEL: Bath and Body Works
NDC: 62670-6129 | Form: AEROSOL, SPRAY
Manufacturer: Bath & Body Works, Inc.
Category: otc | Type: HUMAN OTC DRUG LABEL
Date: 20210813

ACTIVE INGREDIENTS: Aluminum Zirconium Trichlorohydrex GLY 16 g/100 g
INACTIVE INGREDIENTS: Dimethicone

DRUG FACTS

Drug Facts

Active ingredient
Aluminum Zirconium Trichlorohydrex GLY (16%)

Purpose

Antiperspirant

Use

Reduces underarm wetness

Warnings

- For external use only.
- Do not use on broken skin.
- Ask a doctor before use if you have kidney disease.
- Stop use if rash or irritation occurs.

KEEP OUT OF REACH OF CHILDREN

- Keep out of the reach of children. If swallowed, get medical help or contact a Poison Control Center right away.

Directions

Apply to underarms only.

Inactive ingredients

Dimethicone, Stearyl Alcohol,
C15-19 Alkane, Diheptyl Succinate, C12-15 Alkyl Benzoate,
Hydrogenated Castor Oil, Cetyl Alcohol, Water (Aqua, Eau),
Silica, Aluminum Starch Octenylsuccinate, Fragrance
(Parfum), Capryloyl Glycerin/Sebacic Acid Copolymer, Tocopheryl Acetate.